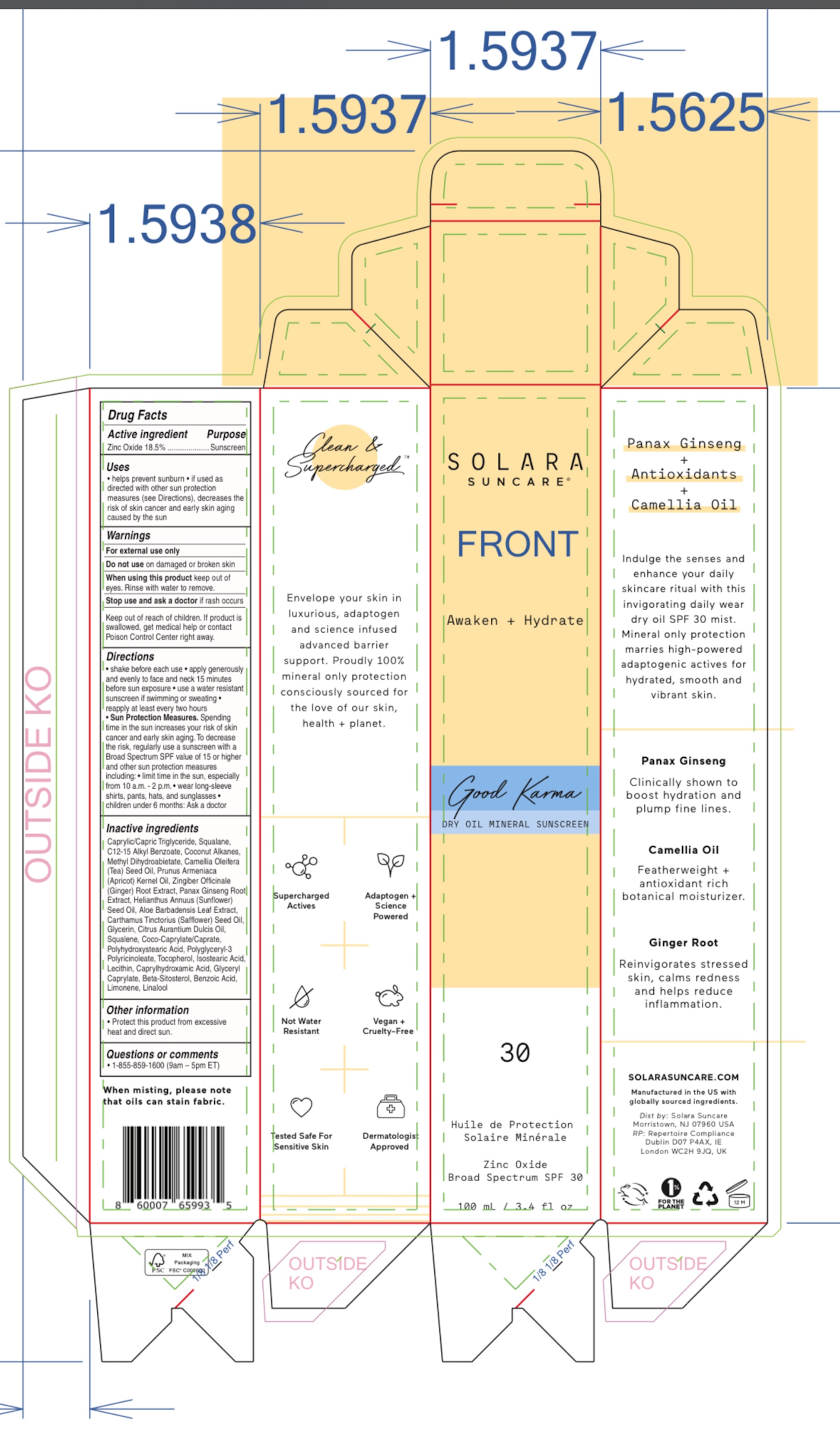 DRUG LABEL: Good Karma Dry Oil Mineral Sunscreen

NDC: 73054-110 | Form: OIL
Manufacturer: SOLARA SUNCARE, INC.
Category: otc | Type: HUMAN OTC DRUG LABEL
Date: 20251231

ACTIVE INGREDIENTS: ZINC OXIDE 18.5 g/100 mL
INACTIVE INGREDIENTS: GLYCERYL CAPRYLATE; .BETA.-SITOSTEROL; ALKYL (C12-15) BENZOATE; POLYGLYCERYL-3 PENTARICINOLEATE; TOCOPHEROL; MEDIUM-CHAIN TRIGLYCERIDES; ALOE VERA LEAF; SQUALENE; POLYHYDROXYSTEARIC ACID (2300 MW); METHYL DIHYDROABIETATE; BENZOIC ACID; ASIAN GINSENG; CITRUS SINENSIS SEED OIL; GINGER; SAFFLOWER OIL; APRICOT KERNEL OIL; SUNFLOWER OIL; CAMELLIA OIL; SOYBEAN LECITHIN; CAPRYLHYDROXAMIC ACID; COCO-CAPRYLATE/CAPRATE; ISOSTEARIC ACID; SQUALANE; COCONUT ALKANES; GLYCERIN; LIMONENE, (+)-

Good Karma Dry Oil Mineral Sunscreen SPF-30

Active ingredients

Zinc Oxide 18.5%

Purpose

Sunscreen

Uses

• helps prevent sunburn
• if used as directed with other sun protection measures (see Directions), decreases the risk of skin cancer and early skin aging caused by the sun

Warnings

For external use only

Do not use

on damaged or broken skin

When using this product

keep out of eyes. Rinse with water to remove.

Stop use and ask a doctor

if a rash occurs

Keep out of reach of children. If product is swallowed, get medical help or contact a Poison Control Center right away

Directions

• shake before each use
• apply generously and evenly to face and neck 15 minutes before sun exposure
• use a water resistant sunscreen if swimming or sweating
• reapply at least every two hours
Sun Protection Measures.Spending time in the sun increases your risk of skin cancer and early skin aging. To decrease the risk, regularly use a sunscreen with a Broad Spectrum SPF value of 15 or higher and other sun protection measures including:
• limit time in the sun, especially from 10 a.m. - 2 p.m.
• wear long-sleeve shirts, pants, hats, and sunglasses
• children under 6 months: Ask a doctor

Other information

• Protect this product from excessive heat or direct sun.

Inactive ingredients

Caprylic/Capric Triglyceride, Squalane, C12-15 Alkyl Benzoate, Coconut Alkanes, Methyl Dihydroabietate, Camellia Oleifera (Tea) Seed Oil, Prunus Armeniaca (Apricot) Kernel Oil, Zingiber Officinale (Ginger) Root Extract, Panax Ginseng Root Extract, Helianthus Annuus (Sunflower) Seed Oil, Aloe Barbadensis Leaf Extract, Carthamus Tinctorius (Safflower) Seed Oil, Glycerin, Citrus Aurantium Dulcis Oil, Squalene, Coco-Caprylate/ Caprate, Polyhydroxystearic Acid, Polyglyceryl-3 Polyricinoleate, Tocopherol, Isostearic Acid, Lecithin, Caprylhydroxamic Acid, Glyceryl Caprylate, Beta-Sitosterol, Benzoic Acid, Limonene, Linalool

Questions or comments

• 1-855-859-1600 (9am - 5pm ET)